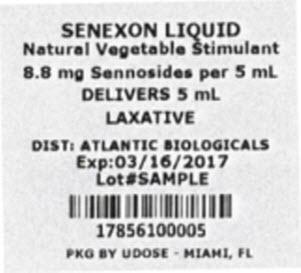 DRUG LABEL: Senexon
NDC: 17856-1000 | Form: SYRUP
Manufacturer: Atlantic Biologicals Corps
Category: otc | Type: HUMAN OTC DRUG LABEL
Date: 20191018

ACTIVE INGREDIENTS: Sennosides A and B 8.8 mg/5 mL
INACTIVE INGREDIENTS: Methylparaben; propylene glycol; propylparaben; water; cocoa; sucrose

Senexon®

Drug Facts

Active ingredient (in each teaspoonful)

Sennosides 8.8 mg

Purpose

Laxative

Uses

- relieves occasional constipation
- generally produces bowel movement in 6-12 hours

Warnings

Do not use

- for longer than one week
- when abdominal pain, nausea or vomiting are present

ASK DOCTOR

noticed a sudden change in bowel habits that lasts over two weeks Ask a doctor before use if you have

ASK DOCTOR/PHARMACIST

taking any other drug. Take this product two or more hours before or after other drugs. Laxatives may affect how other drugs work. Ask a doctor or pharmacist before use if you are

Stop use and ask a doctor if

- you have rectal bleeding
- you fail to have a bowel movement after use of this product. These may indicate a serious condition.

PREGNANCY OR BREAST FEEDING

ask a health professional before use. If pregnant or breast-feeding

KEEP OUT OF REACH OF CHILDREN

In case of overdose, get medical help or contact a Poison Control Center right away. Keep out of reach of children.

Directions

- take preferably at bedtime or as directed by a doctor

age | starting dose | maximum dose
adults and children 12 years and older | 2 - 3 teaspoons once a day | 3 teaspoons twice a day
children 6 to under 12 years | 1 - 1 1/2 teaspoons once a day | 1 1/2 teaspoons twice a day
children 2 to under 6 years | 1/2 - 3/4 teaspoon once a day | 3/4 teaspoon twice a day
children under 2 years | ask a doctor | ask a doctor

Other information

- avoid excessive heat
- store at room temperature 15°- 30°C (59°- 86°F)

Inactive ingredients

cocoa distillate flavor, natural chocolate flavor, methylparaben, propylene glycol, propylparaben, purified water, sucrose

Questions or comments?

Call 1-800-645-2158

Distributed by: Rugby Laboratories 31778 Enterprise Drive Livonia, MI 48150